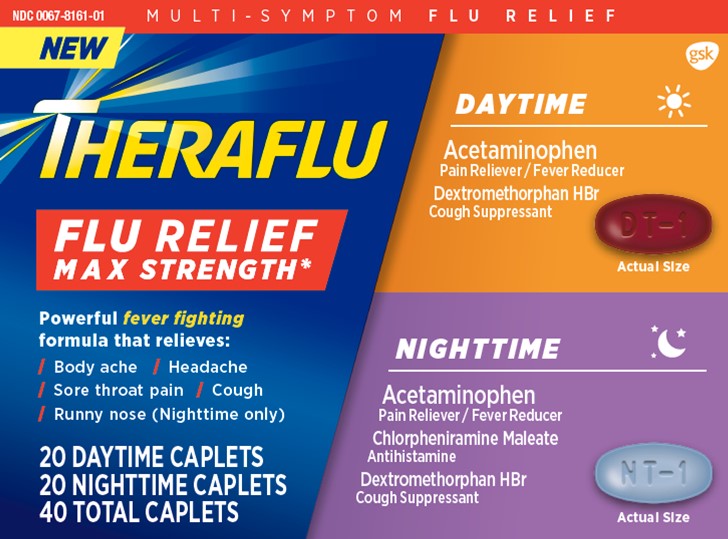 DRUG LABEL: Theraflu Flu Relief Maximum Strength

NDC: 0067-8161 | Form: KIT | Route: ORAL
Manufacturer: Haleon US Holdings LLC
Category: otc | Type: HUMAN OTC DRUG LABEL
Date: 20240308

ACTIVE INGREDIENTS: ACETAMINOPHEN 500 mg/1 1; DEXTROMETHORPHAN HYDROBROMIDE 15 mg/1 1; ACETAMINOPHEN 500 mg/1 1; CHLORPHENIRAMINE MALEATE 2 mg/1 1; DEXTROMETHORPHAN HYDROBROMIDE 15 mg/1 1
INACTIVE INGREDIENTS: CROSPOVIDONE, UNSPECIFIED; D&C YELLOW NO. 10 ALUMINUM LAKE; FD&C RED NO. 40; FD&C YELLOW NO. 6; ALUMINUM OXIDE; MAGNESIUM STEARATE; MICROCRYSTALLINE CELLULOSE; POLYETHYLENE GLYCOL, UNSPECIFIED; POLYVINYL ALCOHOL, UNSPECIFIED; POVIDONE, UNSPECIFIED; STARCH, CORN; SILICON DIOXIDE; SODIUM STARCH GLYCOLATE TYPE A POTATO; STEARIC ACID; TALC; TITANIUM DIOXIDE; CROSPOVIDONE, UNSPECIFIED; FD&C BLUE NO. 2; ALUMINUM OXIDE; MAGNESIUM STEARATE; MICROCRYSTALLINE CELLULOSE; POLYETHYLENE GLYCOL, UNSPECIFIED; POLYVINYL ALCOHOL, UNSPECIFIED; POVIDONE, UNSPECIFIED; SILICON DIOXIDE; SODIUM STARCH GLYCOLATE TYPE A POTATO; STEARIC ACID; TALC; TITANIUM DIOXIDE

Drug Facts

Active ingredients (in each caplet)

Acetaminophen 500 mg

Dextromethorphan HBr 15 mg

Purposes

Pain reliever/Fever reducer

Cough suppressant

Uses

- temporarily relieves these symptoms due to a common cold:
  - headache
  - minor aches and pains
  - cough due to minor throat and bronchial irritation
  - minor sore throat pain
- temporarily reduces fever

Warnings

Liver warning:This product contains acetaminophen. Severe liver damage may occur if you take

- more than 4,000 mg of acetaminophen in 24 hours
- with other drugs containing acetaminophen
- 3 or more alcoholic drinks every day while using this product

Allergy alert:Acetaminophen may cause severe skin reactions. Symptoms may include:

- skin reddening
- blisters
- rash
- If a skin reaction occurs, stop use and seek medical help right away.

Sore throat warning:If sore throat is severe, persists for more than 2 days, is accompanied or followed by fever, headache, rash, nausea, or vomiting consult a doctor promptly.

Do not use

- in a child under 12 years of age
- if you are allergic to acetaminophen
- with any other drug containing acetaminophen (prescription or nonprescription). If you are not sure whether a drug contains acetaminophen, ask a doctor or pharmacist.
- if you are now taking a prescription monoamine oxidase inhibitor (MAOI) (certain drugs for depression, psychiatric, or emotional conditions, or Parkinson’s disease), or for 2 weeks after stopping the MAOI drug. If you do not know if your prescription drug contains an MAOI, ask a doctor or pharmacist before taking this product.

Ask a doctor before use if you have

- liver disease
- a breathing problem such as emphysema or chronic bronchitis
- cough that occurs with too much phlegm (mucus)
- cough that lasts or is chronic such as occurs with smoking, asthma or emphysema

Ask a doctor or pharmacist before use if you are

- taking the blood thinning drug warfarin

Stop use and ask a doctor if

- Pain or cough gets worse or lasts more than 7 days
- fever gets worse or lasts more than 3 days
- redness or swelling is present
- new symptoms occur
- cough comes back or occurs with rash or headache that lasts.
- These could be signs of a serious condition.

If pregnant or breast-feeding,

ask a health professional before use.

Keep out of reach of children.

In case of overdose, get medical help or contact a Poison Control Center right away. Prompt medical attention is critical for adults as well as for children even if you do not notice any signs or symptoms.

Directions

- do not use more than directed
- Adults and children 12 years of age and over: take 2 caplets every 6 hours, while symptoms persist
- do not take more than 6 caplets in 24 hours unless directed by a doctor
- children under 12 years of age: do not use

1. Age

1. Dose

1. adults and children 12 years of age and over

1. 2 caplets every 6 hours

1. children under 12 years of age

1. do not use

Other information

- store at controlled room temperature 20-25°C (68-77°F)

Inactive ingredients

crospovidone, D&C yellow no. 10 aluminum lake, FD&C red no. 40 aluminum lake, FD&C yellow no. 6 aluminum lake, magnesium stearate, microcrystalline cellulose, polyethylene glycol, polyvinyl

alcohol, povidone, pregelatinized starch, silicon dioxide, sodium starch glycolate, stearic acid, talc, titanium dioxide

Questions or comments?

call 1-855-328-5259

Active ingredients (in each caplet)

Acetaminophen 500 mg

Chlorpheniramine maleate 2 mg

Dextromethorphan HBr 15 mg

Purposes

Pain Reliever/Fever reducer

Antihistamine

Cough suppressant

Uses

- temporarily relieves these symptoms due to a common cold:
  - Headache
  - minor aches and pains
  - cough due to minor throat and bronchial irritation
  - minor sore throat pain
  - runny nose
- temporarily reduces fever

Warnings

Liver warning:This product contains acetaminophen. Severe liver damage may occur if you take

- more than 4,000 mg of acetaminophen in 24 hours
- with other drugs containing acetaminophen
- 3 or more alcoholic drinks every day while using this product

Allergy alert:Acetaminophen may cause severe skin reactions. Symptoms may include:

- skin reddening
- blisters
- rash

If a skin reaction occurs, stop use and seek medical help right away.

Sore throat warning:If sore throat is severe, persists for more than 2 days, is accompanied or followed by fever, headache, rash, nausea, or vomiting consult a doctor promptly.

Do not use

- in a child under 12 years of age
- if you are allergic to acetaminophen
- with any other drug containing acetaminophen (prescription or nonprescription). If you are not sure whether a drug contains acetaminophen, ask a doctor or pharmacist.
- if you are now taking a prescription monoamine oxidase inhibitor (MAOI) (certain drugs for depression, psychiatric, or emotional conditions, or Parkinson’s disease), or for 2 weeks after stopping the MAOI drug. If you do not know if your prescription drug contains a MAO, ask a doctor or pharmacist before taking this product.

Ask a doctor before use if you have

- liver disease
- a breathing problem such as emphysema or chronic bronchitis
- glaucoma
- trouble urinating due to an enlarged prostate gland
- cough that occurs with too much phlegm (mucus)
- cough that lasts or is chronic such as occurs with smoking, asthma, or emphysema

Ask a doctor or pharmacist before use if you are

- taking the blood thinning drug warfarin
- taking sedatives or tranquilizers

When using this product

- avoid alcoholic drinks
- marked drowsiness may occur
- alcohol, sedatives, and tranquilizers may increase drowsiness
- be careful when driving a motor vehicle or operating machinery
- excitability may occur, especially in children

Stop use and ask a doctor if

- pain or cough gets worse or lasts more than 7 days
- fever gets worse or lasts more than 3 days
- redness or swelling is present
- new symptoms occur
- cough comes back or occurs with rash or headache that lasts.
- These could be signs of a serious condition.

If pregnant or breast-feeding,

ask a health professional before use.

Keep out of reach of children.

In case of overdose, get medical help or contact a Poison Control Center right away. Prompt medical attention is critical for adults as well as for children even if you do not notice any signs or symptoms.

Directions

- do not use more than directed
- Adults and children 12 years of age and over: take 2 caplets every 6 hours, while symptoms persist
- do not take more than 6 caplets in 24 hours unless directed by a doctor
- children under 12 years of age: do not use

1. Age

1. Dose

1. adults and children 12 years of age and over

1. 2 caplets every 6 hours

1. children under 12 years of age

1. do not use

Other information

- store at controlled room temperature 20-25°C (68-77°F)

Inactive ingredients

crospovidone, FD&C blue no. 2 aluminum lake, magnesium stearate, microcrystalline cellulose, polyethylene glycol, polyvinyl alcohol, povidone, pregelatinized starch, silicon dioxide, sodium starch

glycolate, stearic acid, talc, titanium dioxide

Questions or comments?

1-855-328-5259

Other Safety Information

DO NOT TAKE THE DAYTIME AND NIGHTTIME PRODUCTS AT THE SAME TIME.

DO NOT TAKE MORE THAN 3 DOSES IN TOTAL IN ANY 24 HOUR PERIOD.

PARENTS:Learn about teen medicine abuse

www.StopMedicineAbuse.org

*Maximum Strength per 6 hour dose.

TAMPER-EVIDENT FEATURE: THERAFLU FLU RELIEF MAX STRENGTH CAPLETS ARE SEALED IN BLISTER PACKETS. USE ONLY IF THE INDIVIDUAL SEAL IS UNBROKEN.

READ ALLWARNINGS AND DIRECTIONS ON CARTON BEFORE USE.

KEEP CARTON FOR REFERENCE. DO NOT DISCARD.

DO NOT TAKE A DOSE OF THE NIGHTTIME PRODUCT SOONER THAN 6 HOURS AFTER THE LAST DOSE OF THE DAYTIME PRODUCT UNLESS DIRECTED BY YOUR DOCTOR.

DO NOT TAKE THE DAYTIME AND NIGHTTIME PRODUCTS AT THE SAME TIME.

DO NOT TAKE MORE THAN 3 DOSES IN TOTAL IN ANY 24 HOUR PERIOD.

Distributed by: GSK Consumer Healthcare

Warren, NJ 07059

Trademarks are owned by or licensed to the GSK group of companies.

©2022 GSK group of companies or its licensor.

B-0630-770771-10 REV A

Principal Display Panel

NDC 0067-8161-01

THERAFLU

FLU RELIEF

MAX STRENGTH*

MULTI-SYMPTOM FLU RELIEF

Powerful fever fightingformula that relieves:

/ Body ache / Headache

/ Sore throat pain / cough

/ Runny nose (Nighttime only)

DAYTIME

Acetaminophen

Pain Reliever / Fever Reducer

Dextromethorphan HBr

Cough Suppressant

NIGHTTIME

Acetaminophen

Pain Reliever / Fever Reducer

Chlorpheniramine Maleate

Antihistamine

Dextromethorphan HBr

Cough Suppressant

20 DAYTIME CAPLETS

20 NIGHTTIME CAPLETS

40 TOTAL CAPLETS